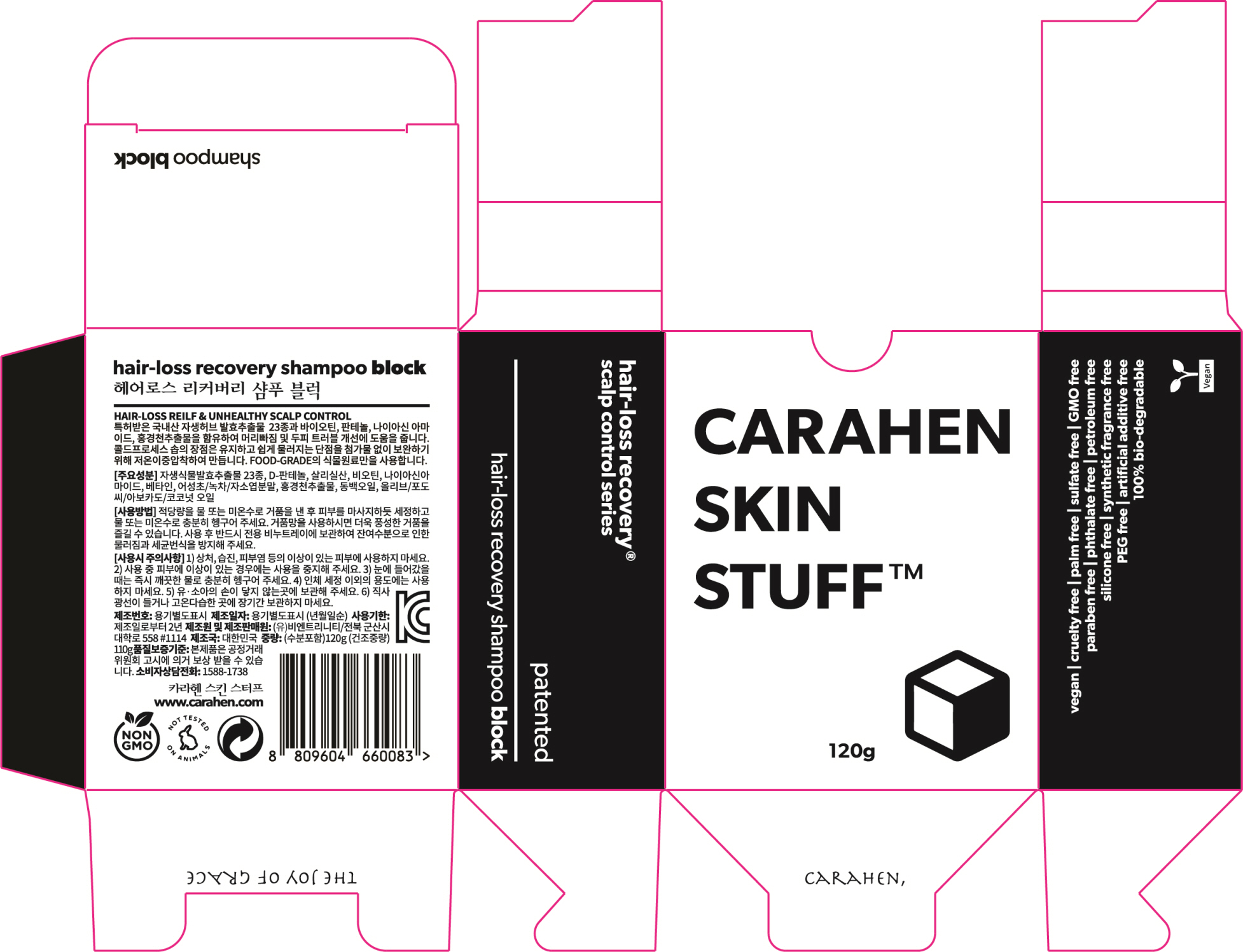 DRUG LABEL: hair-loss recovery shampooblock
NDC: 71583-0004 | Form: SOAP
Manufacturer: B.N.Trinity Co.,Ltd
Category: otc | Type: HUMAN OTC DRUG LABEL
Date: 20180710

ACTIVE INGREDIENTS: SALICYLIC ACID 0.4 g/100 g
INACTIVE INGREDIENTS: NIACINAMIDE

Drug Facts

ACTIVE INGREDIENT

Salicylic Acid

INACTIVE INGREDIENT

Niacinamide, etc

PURPOSE

Helps to scalp revitalizing and hair-loss recovery

keep out of reach of the children

INDICATIONS AND USAGE

After bubbling this product with water or lukewarm water, massage it to scalp.

WARNINGS

1. Do not use in the following cases(Eczema and scalp wounds)
2.Side Effects
1)Due to the use of this druf if rash, irritation, itching and symptopms of hypersnesitivity occur dicontinue use and consult your phamacisr or doctor
3.General Precautions
1)If in contact with the eyes, wash out thoroughty with water If the symptoms are servere, seek medical advice immediately
2)This product is for exeternal use only. Do not use for internal use
4.Storage and handling precautions
1)If possible, avoid direct sunlight and store in cool and area of low humidity
2)In order to maintain the quality of the product and avoid misuse
3)Avoid placing the product near fire and store out in reach of children

DOSAGE AND ADMINISTRATION

for external use only